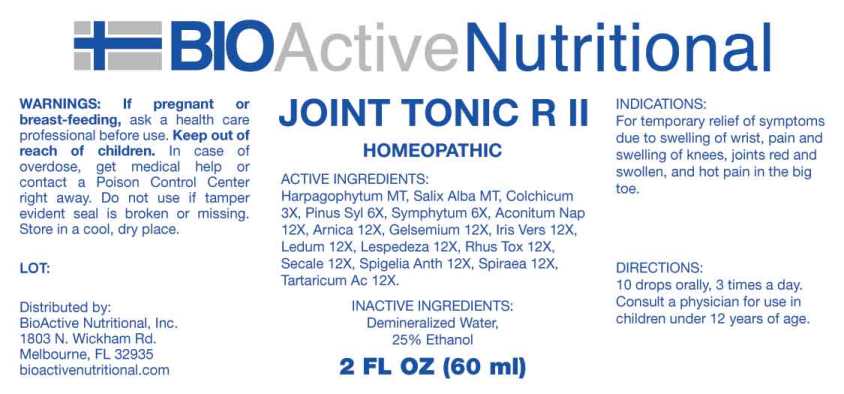 DRUG LABEL: Joint Tonic R
NDC: 43857-0588 | Form: LIQUID
Manufacturer: BioActive Nutritional, Inc.
Category: homeopathic | Type: HUMAN OTC DRUG LABEL
Date: 20241017

ACTIVE INGREDIENTS: HARPAGOPHYTUM PROCUMBENS ROOT 1 [hp_X]/1 mL; SALIX ALBA BARK 1 [hp_X]/1 mL; COLCHICUM AUTUMNALE BULB 3 [hp_X]/1 mL; PINUS SYLVESTRIS LEAFY TWIG 6 [hp_X]/1 mL; COMFREY ROOT 6 [hp_X]/1 mL; ACONITUM NAPELLUS WHOLE 12 [hp_X]/1 mL; ARNICA MONTANA WHOLE 12 [hp_X]/1 mL; GELSEMIUM SEMPERVIRENS ROOT 12 [hp_X]/1 mL; IRIS VERSICOLOR ROOT 12 [hp_X]/1 mL; RHODODENDRON TOMENTOSUM LEAFY TWIG 12 [hp_X]/1 mL; LESPEDEZA CAPITATA FLOWERING TOP 12 [hp_X]/1 mL; TOXICODENDRON PUBESCENS LEAF 12 [hp_X]/1 mL; CLAVICEPS PURPUREA SCLEROTIUM 12 [hp_X]/1 mL; SPIGELIA ANTHELMIA WHOLE 12 [hp_X]/1 mL; FILIPENDULA ULMARIA ROOT 12 [hp_X]/1 mL; TARTARIC ACID 12 [hp_X]/1 mL
INACTIVE INGREDIENTS: WATER; ALCOHOL

DRUG FACTS:

ACTIVE INGREDIENTS:

Harpagophytum Procumbens MT, Salix Alba MT, Colchicum Autumnale 3X, Pinus Sylvestris 6X, Symphytum Officinale 6X, Aconitum Napellus 12X, Arnica Montana 12X, Gelsemium Sempervirens 12X, Iris Versicolor 12X, Ledum Palustre 12X, Lespedeza Capitata 12X, Rhus Tox 12X, Secale Cornutum 12X, Spigelia Anthelmia 12X, Spiraea Ulmaria 12X, Tartaricum Acidum 12X.

INDICATIONS:

For temporary relief of symptoms due to swelling of wrist, pain and swelling of knees, joints red and swollen, and hot pain in the big toe.

WARNINGS:

If pregnant or breast-feeding, ask a health care professional before use.

Keep out of reach of children. In case of overdose, get medical help or contact a Poison Control Center right away.

Do not use if tamper evident seal is broken or missing.

Store in cool, dry place.

Keep out of reach of children. In case of overdose, get medical help or contact a Poison Control Center right away.

DIRECTIONS:

10 drops orally, 3 times a day. Consult a physician for use in children under 12 years of age.

INDICATIONS:

For temporary relief of symptoms due to swelling of wrist, pain and swelling of knees, joints red and swollen, and hot pain in the big toe.

INACTIVE INGREDIENTS:

Demineralized Water, 25% Ethanol

QUESTIONS:

Distributed by:

BioActive Nutritional, Inc.

1803 N. Wickham Rd.

Melbourne, FL 32935

bioactivenutritional.com

PACKAGE LABEL DISPLAY:

BIOActive Nutritional

JOINT TONIC R II

HOMEOPATHIC

2 FL OZ (60 ml)